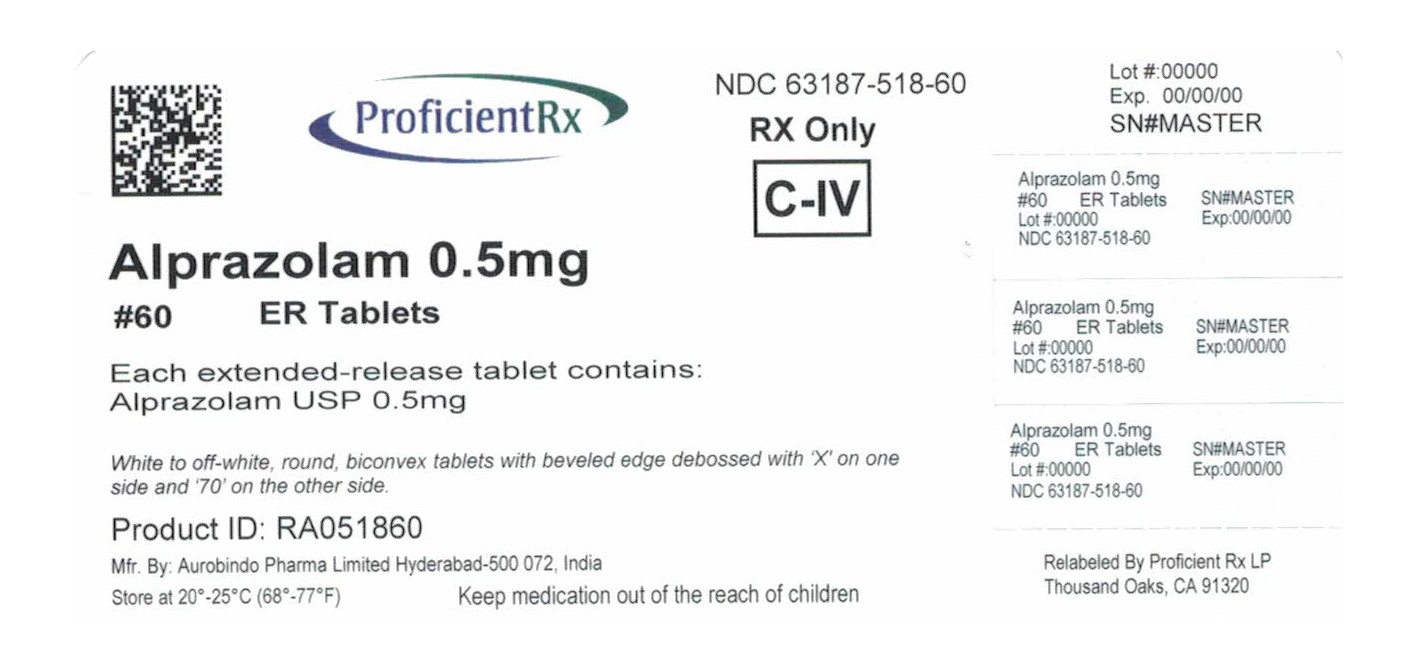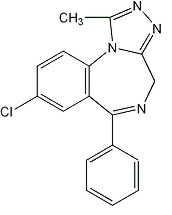 DRUG LABEL: Alprazolam
NDC: 63187-518 | Form: TABLET, EXTENDED RELEASE
Manufacturer: Proficient Rx LP
Category: prescription | Type: HUMAN PRESCRIPTION DRUG LABEL
Date: 20210101
DEA Schedule: CIV

ACTIVE INGREDIENTS: ALPRAZOLAM 0.5 mg/1 1
INACTIVE INGREDIENTS: SILICON DIOXIDE; HYPROMELLOSE 2208 (4000 MPA.S); HYPROMELLOSE 2208 (100 MPA.S); LACTOSE MONOHYDRATE; MAGNESIUM STEARATE

Alprazolam Extended-Release Tablets USP CIV
Rx only

DESCRIPTION

Alprazolam extended-releasetablets USP contain alprazolam which is a triazolo analog of the 1,4 benzodiazepine class of central nervous system-active compounds.

The chemical name of alprazolam is 8-chloro-1-methyl-6-phenyl-4H-s-triazolo [4,3-α] [1,4] benzodiazepine. The molecular formula is C17H13ClN4 which corresponds to a molecular weight of 308.76.

The structural formula is represented below:

Alprazolam USP is a white to off-white, crystalline powder, which is soluble in methanol or ethanol but which has no appreciable solubility in water at physiological pH.

Each alprazolam extended-release tablet USP, for oral administration, contains 0.5 mg, 1 mg, 2 mg, or 3 mg of alprazolam. The inactive ingredients are colloidal silicon dioxide, hypromellose, lactose monohydrate, and magnesium stearate. In addition, the 1 mg and 3 mg tablets contain D&C Yellow No. 10 aluminum lake and the 2 mg and 3 mg tablets contain FD&C Blue No. 2 lake.

Meets USP Dissolution Test 4.

CLINICAL PHARMACOLOGY

Pharmacodynamics
CNS agents of the 1,4 benzodiazepine class presumably exert their effects by binding at stereospecific receptors at several sites within the central nervous system. Their exact mechanism of action is unknown. Clinically, all benzodiazepines cause a dose-related central nervous system depressant activity varying from mild impairment of task performance to hypnosis.
Pharmacokinetics
Absorption
Following oral administration of alprazolam (immediate-release) tablets, alprazolam is readily absorbed. Peak concentrations in the plasma occur in one to two hours following administration. Plasma levels are proportional to the dose given; over the dose range of 0.5 to 3 mg, peak levels of 8 to 37 ng/mL were observed. Using a specific assay methodology, the mean plasma elimination half-life of alprazolam has been found to be about 11.2 hours (range: 6.3 to 26.9 hours) in healthy adults.
The mean absolute bioavailability of alprazolam from alprazolam extended-release tablets is approximately 90%, and the relative bioavailability compared to alprazolam tablets is 100%. The bioavailability and pharmacokinetics of alprazolam following administration of alprazolam extended-release tablets are similar to that for alprazolam tablets, with the exception of a slower rate of absorption. The slower absorption rate results in a relatively constant concentration that is maintained between 5 and 11 hours after the dosing. The pharmacokinetics of alprazolam and two of its major active metabolites (4-hydroxyalprazolam and α-hydroxyalprazolam) are linear, and concentrations are proportional up to the recommended maximum daily dose of 10 mg given once daily. Multiple dose studies indicate that the metabolism and elimination of alprazolam are similar for the immediate-release and the extended-release products.
Food has a significant influence on the bioavailability of alprazolam extended-release tablets. A high-fat meal given up to 2 hours before dosing with alprazolam extended-release tablets increased the mean Cmax by about 25%. The effect of this meal on Tmax depended on the timing of the meal, with a reduction in Tmax by about 1/3 for subjects eating immediately before dosing and an increase in Tmax by about 1/3 for subjects eating 1 hour or more after dosing. The extent of exposure (AUC) and elimination half-life (t1/2) were not affected by eating.
There were significant differences in absorption rate for the alprazolam extended-release tablet, depending on the time of day administered, with the Cmax increased by 30% and the Tmax decreased by an hour following dosing at night, compared to morning dosing.
Distribution
The apparent volume of distribution of alprazolam is similar for alprazolam extended-release and alprazolam tablets. In vitro, alprazolam is bound (80%) to human serum protein. Serum albumin accounts for the majority of the binding.
Metabolism
Alprazolam is extensively metabolized in humans, primarily by cytochrome P450 3A4 (CYP3A4), to two major metabolites in the plasma: 4-hydroxyalprazolam and α-hydroxyalprazolam. A benzophenone derived from alprazolam is also found in humans. Their half-lives appear to be similar to that of alprazolam. The pharmacokinetic parameters at steady-state for the two hydroxylated metabolites of alprazolam (4-hydroxyalprazolam and α-hydroxyalprazolam) were similar for alprazolam and alprazolam extended-release tablets, indicating that the metabolism of alprazolam is not affected by absorption rate. The plasma concentrations of 4-hydroxyalprazolam and α-hydroxyalprazolam relative to unchanged alprazolam concentration after both alprazolam extended-release and alprazolam tablets were always less than 10% and 4%, respectively. The reported relative potencies in benzodiazepine receptor binding experiments and in animal models of induced seizure inhibition are 0.2 and 0.66, respectively, for 4-hydroxyalprazolam and α-hydroxyalprazolam. Such low concentrations and the lesser potencies of 4-hydroxyalprazolam and α-hydroxyalprazolam suggest that they are unlikely to contribute much to the pharmacological effects of alprazolam. The benzophenone metabolite is essentially inactive.
Elimination
Alprazolam and its metabolites are excreted primarily in the urine. The mean plasma elimination half-life of alprazolam following administration of alprazolam extended-release tablet ranges from 10.7 to 15.8 hours in healthy adults.
Special Populations
While pharmacokinetic studies have not been performed in special populations with alprazolam extended-release tablets, the factors (such as age, gender, hepatic or renal impairment) that would affect the pharmacokinetics of alprazolam after the administration of alprazolam tablets would not be expected to be different with the administration of alprazolam extended-release tablets.
Changes in the absorption, distribution, metabolism, and excretion of benzodiazepines have been reported in a variety of disease states including alcoholism, impaired hepatic function, and impaired renal function. Changes have also been demonstrated in geriatric patients. A mean half-life of alprazolam of 16.3 hours has been observed in healthy elderly subjects (range: 9 to 26.9 hours, n=16) compared to 11 hours (range: 6.3 to 15.8 hours, n=16) in healthy adult subjects. In patients with alcoholic liver disease the half-life of alprazolam ranged between 5.8 and 65.3 hours (mean: 19.7 hours, n=17) as compared to between 6.3 and 26.9 hours (mean=11.4 hours, n=17) in healthy subjects. In an obese group of subjects the half-life of alprazolam ranged between 9.9 and 40.4 hours (mean=21.8 hours, n=12) as compared to between 6.3 and 15.8 hours (mean=10.6 hours, n=12) in healthy subjects.
Because of its similarity to other benzodiazepines, it is assumed that alprazolam undergoes transplacental passage and that it is excreted in human milk.
Race — Maximal concentrations and half-life of alprazolam are approximately 15% and 25% higher in Asians compared to Caucasians.
Pediatrics — The pharmacokinetics of alprazolam after administration of the alprazolam extended-release tablet in pediatric patients have not been studied.
Gender — Gender has no effect on the pharmacokinetics of alprazolam.
Cigarette Smoking — Alprazolam concentrations may be reduced by up to 50% in smokers compared to non-smokers.
Drug-Drug Interactions
Alprazolam is primarily eliminated by metabolism via cytochrome P450 3A (CYP3A). Most of the interactions that have been documented with alprazolam are with drugs that inhibit or induce CYP3A4.
Compounds that are potent inhibitors of CYP3A would be expected to increase plasma alprazolam concentrations. Drug products that have been studied in vivo, along with their effect on increasing alprazolam AUC, are as follows: ketoconazole, 3.98 fold; itraconazole, 2.7 fold; nefazodone, 1.98 fold; fluvoxamine, 1.96 fold; and erythromycin, 1.61 fold (see CONTRAINDICATIONS, WARNINGS, and PRECAUTIONS–Drug Interactions).
CYP3A inducers would be expected to decrease alprazolam concentrations and this has been observed in vivo. The oral clearance of alprazolam (given in a 0.8 mg single dose) was increased from 0.9±0.21 mL/min/kg to 2.13±0.54 mL/min/kg and the elimination t1/2 was shortened (from 17.1±4.9 to 7.7±1.7 h) following administration of 300 mg/day carbamazepine for 10 days (see PRECAUTIONS–Drug Interactions). However, the carbamazepine dose used in this study was fairly low compared to the recommended doses (1000 to 1200 mg/day); the effect at usual carbamazepine doses is unknown.
The ability of alprazolam to induce or inhibit human hepatic enzyme systems has not been determined. However, this is not a property of benzodiazepines in general. Further, alprazolam did not affect the prothrombin or plasma warfarin levels in male volunteers administered sodium warfarin orally.

CLINICAL EFFICACY TRIALS

The efficacy of alprazolam extended-release tablets in the treatment of panic disorder was established in two 6-week, placebo-controlled studies of alprazolam extended-release in patients with panic disorder.
In two 6-week, flexible-dose, placebo-controlled studies in patients meeting DSM-III criteria for panic disorder, patients were treated with alprazolam extended-release in a dose range of 1 to 10 mg/day, on a once-a-day basis. The effectiveness of alprazolam extended-release was assessed on the basis of changes in various measures of panic attack frequency, on various measures of the Clinical Global Impression, and on the Overall Phobia Scale. In all, there were seven primary efficacy measures in these studies, and alprazolam extended-release was superior to placebo on all seven outcomes in both studies. The mean dose of alprazolam extended-release at the last treatment visit was 4.2 mg/day in the first study and 4.6 mg/day in the second.
In addition, there were two 8-week, fixed-dose, placebo-controlled studies of alprazolam extended-release in patients with panic disorder, involving fixed alprazolam extended-release doses of 4 and 6 mg/day, on a once-a-day basis, that did not show a benefit for either dose of alprazolam extended-release.
The longer-term efficacy of alprazolam extended-release in panic disorder has not been systematically evaluated.
Analyses of the relationship between treatment outcome and gender did not suggest any differential responsiveness on the basis of gender.

INDICATIONS AND USAGE

Alprazolam extended-release tablets USP are indicated for the treatment of panic disorder, with or without agoraphobia.
This claim is supported on the basis of two positive studies with alprazolam extended-release tablets USP conducted in patients whose diagnoses corresponded closely to the DSM-III-R/IV criteria for panic disorder (see CLINICAL EFFICACY TRIALS).
Panic disorder (DSM-IV) is characterized by recurrent unexpected panic attacks, i.e., a discrete period of intense fear or discomfort in which four (or more) of the following symptoms develop abruptly and reach a peak within 10 minutes: (1) palpitations, pounding heart, or accelerated heart rate; (2) sweating; (3) trembling or shaking; (4) sensations of shortness of breath or smothering; (5) feeling of choking; (6) chest pain or discomfort; (7) nausea or abdominal distress; (8) feeling dizzy, unsteady, lightheaded, or faint; (9) derealization (feelings of unreality) or depersonalization (being detached from oneself); (10) fear of losing control; (11) fear of dying; (12) paresthesias (numbness or tingling sensations); (13) chills or hot flushes.
The longer-term efficacy of alprazolam extended-release tablets USP has not been systematically evaluated. Thus, the physician who elects to use this drug for periods longer than 8 weeks should periodically reassess the usefulness of the drug for the individual patient.

CONTRAINDICATIONS

Alprazolam extended-release tablets are contraindicated in patients with known sensitivity to this drug or other benzodiazepines. Alprazolam extended-release tablets may be used in patients with open angle glaucoma who are receiving appropriate therapy, but is contraindicated in patients with acute narrow angle glaucoma.
Alprazolam extended-release tablets are contraindicated with ketoconazole and itraconazole, since these medications significantly impair the oxidative metabolism mediated by cytochrome P450 3A (CYP3A) (see CLINICAL PHARMACOLOGY, WARNINGS and PRECAUTIONS–Drug Interactions).

WARNINGS

Dependence and Withdrawal Reactions, Including Seizures
Certain adverse clinical events, some life-threatening, are a direct consequence of physical dependence to alprazolam. These include a spectrum of withdrawal symptoms; the most important is seizure (see DRUG ABUSE AND DEPENDENCE). Even after relatively short-term use at doses of ≤ 4 mg/day, there is some risk of dependence. Spontaneous reporting system data suggest that the risk of dependence and its severity appear to be greater in patients treated with doses greater than 4 mg/day and for long periods (more than 12 weeks). However, in a controlled postmarketing discontinuation study of panic disorder patients who received alprazolam tablets, the duration of treatment (3 months compared to 6 months) had no effect on the ability of patients to taper to zero dose. In contrast, patients treated with doses of alprazolam tablets greater than 4 mg/day had more difficulty tapering to zero dose than those treated with less than 4 mg/day.
Relapse or return of illness was defined as a return of symptoms characteristic of panic disorder (primarily panic attacks) to levels approximately equal to those seen at baseline before active treatment was initiated. Rebound refers to a return of symptoms of panic disorder to a level substantially greater in frequency, or more severe in intensity than seen at baseline. Withdrawal symptoms were identified as those which were generally not characteristic of panic disorder and which occurred for the first time more frequently during discontinuation than at baseline.
The rate of relapse, rebound, and withdrawal in patients with panic disorder who received alprazolam extended-release tablets has not been systematically studied. Experience in randomized placebo-controlled discontinuation studies of patients with panic disorder who received alprazolam tablets showed a high rate of rebound and withdrawal symptoms compared to placebo treated patients.
In a controlled clinical trial in which 63 patients were randomized to alprazolam tablets and where withdrawal symptoms were specifically sought, the following were identified as symptoms of withdrawal: heightened sensory perception, impaired concentration, dysosmia, clouded sensorium, paresthesias, muscle cramps, muscle twitch, diarrhea, blurred vision, appetite decrease, and weight loss. Other symptoms, such as anxiety and insomnia, were frequently seen during discontinuation, but it could not be determined if they were due to return of illness, rebound, or withdrawal.
In two controlled trials of 6 to 8 weeks duration where the ability of patients to discontinue medication was measured, 71% to 93% of patients treated with alprazolam tablets tapered completely off therapy compared to 89% to 96% of placebo treated patients. In a controlled postmarketing discontinuation study of panic disorder patients treated with alprazolam tablets, the duration of treatment (3 months compared to 6 months) had no effect on the ability of patients to taper to zero dose.
Seizures were reported for three patients in panic disorder clinical trials with alprazolam extended-release. In two cases, the patients had completed 6 weeks of treatment with alprazolam extended-release 6 mg/day before experiencing a single seizure. In one case, the patient abruptly discontinued alprazolam extended-release, and in both cases, alcohol intake was implicated. The third case involved multiple seizures after the patient completed treatment with alprazolam extended-release 4 mg/day and missed taking the medication on the first day of taper. All three patients recovered without sequelae.
Seizures have also been observed in association with dose reduction or discontinuation of alprazolam tablets, the immediate release form of alprazolam. Seizures attributable to alprazolam were seen after drug discontinuance or dose reduction in 8 of 1980 patients with panic disorder or in patients participating in clinical trials where doses of alprazolam greater than 4 mg/day for over 3 months were permitted. Five of these cases clearly occurred during abrupt dose reduction, or discontinuation from daily doses of 2 to 10 mg. Three cases occurred in situations where there was not a clear relationship to abrupt dose reduction or discontinuation. In one instance, seizure occurred after discontinuation from a single dose of 1 mg after tapering at a rate of 1 mg every three days from 6 mg daily. In two other instances, the relationship to taper is indeterminate; in both of these cases the patients had been receiving doses of 3 mg daily prior to seizure. The duration of use in the above 8 cases ranged from 4 to 22 weeks. There have been occasional voluntary reports of patients developing seizures while apparently tapering gradually from alprazolam. The risk of seizure seems to be greatest 24 to 72 hours after discontinuation (see DOSAGE AND ADMINISTRATION for recommended tapering and discontinuation schedule).
Status Epilepticus
The medical event voluntary reporting system shows that withdrawal seizures have been reported in association with the discontinuation of alprazolam tablets. In most cases, only a single seizure was reported; however, multiple seizures and status epilepticus were reported as well.
Interdose Symptoms
Early morning anxiety and emergence of anxiety symptoms between doses of alprazolam tablets have been reported in patients with panic disorder taking prescribed maintenance doses. These symptoms may reflect the development of tolerance or a time interval between doses which is longer than the duration of clinical action of the administered dose. In either case, it is presumed that the prescribed dose is not sufficient to maintain plasma levels above those needed to prevent relapse, rebound, or withdrawal symptoms over the entire course of the interdosing interval.
Risk of Dose Reduction
Withdrawal reactions may occur when dosage reduction occurs for any reason. This includes purposeful tapering, but also inadvertent reduction of dose (e.g., the patient forgets, the patient is admitted to a hospital). Therefore, the dosage of alprazolam extended-release should be reduced or discontinued gradually (see DOSAGE AND ADMINISTRATION).
CNS Depression and Impaired Performance
Because of its CNS depressant effects, patients receiving alprazolam extended-release should be cautioned against engaging in hazardous occupations or activities requiring complete mental alertness such as operating machinery or driving a motor vehicle. For the same reason, patients should be cautioned about the simultaneous ingestion of alcohol and other CNS depressant drugs during treatment with alprazolam extended-release.
Risk of Fetal Harm
Benzodiazepines can potentially cause fetal harm when administered to pregnant women. If alprazolam is used during pregnancy, or if the patient becomes pregnant while taking this drug, the patient should be apprised of the potential hazard to the fetus. Because of experience with other members of the benzodiazepine class, alprazolam is assumed to be capable of causing an increased risk of congenital abnormalities when administered to a pregnant woman during the first trimester. Because use of these drugs is rarely a matter of urgency, their use during the first trimester should almost always be avoided. The possibility that a woman of childbearing potential may be pregnant at the time of institution of therapy should be considered. Patients should be advised that if they become pregnant during therapy or intend to become pregnant they should communicate with their physicians about the desirability of discontinuing the drug.
Alprazolam Interaction With Drugs That Inhibit Metabolism Via Cytochrome P450 3A
The initial step in alprazolam metabolism is hydroxylation catalyzed by cytochrome P450 3A (CYP3A). Drugs that inhibit this metabolic pathway may have a profound effect on the clearance of alprazolam. Consequently, alprazolam should be avoided in patients receiving very potent inhibitors of CYP3A. With drugs inhibiting CYP3A to a lesser but still significant degree, alprazolam should be used only with caution and consideration of appropriate dosage reduction. For some drugs, an interaction with alprazolam has been quantified with clinical data; for other drugs, interactions are predicted from in vitro data and/or experience with similar drugs in the same pharmacologic class.
The following are examples of drugs known to inhibit the metabolism of alprazolam and/or related benzodiazepines, presumably through inhibition of CYP3A.
Potent CYP3A Inhibitors
Azole antifungal agents — Ketoconazole and itraconazole are potent CYP3A inhibitors and have been shown in vivo to increase plasma alprazolam concentrations 3.98 fold and 2.7 fold, respectively. The coadministration of alprazolam with these agents is not recommended. Other azole-type antifungal agents should also be considered potent CYP3A inhibitors and the coadministration of alprazolam with them is not recommended (see CONTRAINDICATIONS).
Drugs demonstrated to be CYP3A inhibitors on the basis of clinical studies involving alprazolam (caution and consideration of appropriate alprazolam dose reduction are recommended during coadministration with the following drugs)
Nefazodone — Coadministration of nefazodone increased alprazolam concentration two-fold.
Fluvoxamine — Coadministration of fluvoxamine approximately doubled the maximum plasma concentration of alprazolam, decreased clearance by 49%, increased half-life by 71%, and decreased measured psychomotor performance.
Cimetidine — Coadministration of cimetidine increased the maximum plasma concentration of alprazolam by 86%, decreased clearance by 42%, and increased half-life by 16%.
Other Drugs Possibly Affecting Alprazolam Metabolism
Other drugs possibly affecting alprazolam metabolism by inhibition of CYP3A are discussed in the PRECAUTIONS section (see PRECAUTIONS–Drug Interactions).

PRECAUTIONS

General

Suicide
As with other psychotropic medications, the usual precautions with respect to administration of the drug and size of the prescription are indicated for severely depressed patients or those in whom there is reason to expect concealed suicidal ideation or plans. Panic disorder has been associated with primary and secondary major depressive disorders and increased reports of suicide among untreated patients.
Mania
Episodes of hypomania and mania have been reported in association with the use of alprazolam tablets in patients with depression.
Uricosuric Effect
Alprazolam has a weak uricosuric effect. Although other medications with weak uricosuric effect have been reported to cause acute renal failure, there have been no reported instances of acute renal failure attributable to therapy with alprazolam.
Use in Patients with Concomitant Illness
It is recommended that the dosage be limited to the smallest effective dose to preclude the development of ataxia or oversedation which may be a particular problem in elderly or debilitated patients (see DOSAGE AND ADMINISTRATION). The usual precautions in treating patients with impaired renal, hepatic, or pulmonary function should be observed. There have been rare reports of death in patients with severe pulmonary disease shortly after the initiation of treatment with alprazolam tablets. A decreased systemic alprazolam elimination rate (e.g., increased plasma half-life) has been observed in both alcoholic liver disease patients and obese patients receiving alprazolam tablets (see CLINICAL PHARMACOLOGY).

Information for Patients

To assure safe and effective use of alprazolam extended-release, the physician should provide the patient with the following guidance.

- Inform your physician about any alcohol consumption and medicine you are taking now, including medication you may buy without a prescription. Alcohol should generally not be used during treatment with benzodiazepines.
- Not recommended for use in pregnancy. Therefore, inform your physician if you are pregnant, if you are planning to have a child, or if you become pregnant while you are taking this medication.
- Inform your physician if you are nursing.
- Until you experience how this medication affects you, do not drive a car or operate potentially dangerous machinery, etc.
- Do not increase the dose even if you think the medication “does not work anymore” without consulting your physician. Benzodiazepines, even when used as recommended, may produce emotional and/or physical dependence.
- Do not stop taking this medication abruptly or decrease the dose without consulting your physician, since withdrawal symptoms can occur.
- Some patients may find it very difficult to discontinue treatment with alprazolam extended-release due to severe emotional and physical dependence. Discontinuation symptoms, including possible seizures, may occur following discontinuation from any dose, but the risk may be increased with extended use at doses greater than 4 mg/day, especially if discontinuation is too abrupt. It is important that you seek advice from your physician to discontinue treatment in a careful and safe manner. Proper discontinuation will help to decrease the possibility of withdrawal reactions that can range from mild reactions to severe reactions such as seizure.

Laboratory Tests

Laboratory tests are not ordinarily required in otherwise healthy patients. However, when treatment is protracted, periodic blood counts, urinalysis, and blood chemistry analyses are advisable in keeping with good medical practice.

Drug Interactions

Use with Other CNS Depressants
If alprazolam extended-release tablets are to be combined with other psychotropic agents or anticonvulsant drugs, careful consideration should be given to the pharmacology of the agents to be employed, particularly with compounds which might potentiate the action of benzodiazepines. The benzodiazepines, including alprazolam, produce additive CNS depressant effects when coadministered with other psychotropic medications, anticonvulsants, antihistaminics, ethanol and other drugs which themselves produce CNS depression.
Use with Imipramine and Desipramine
The steady state plasma concentrations of imipramine and desipramine have been reported to be increased an average of 31% and 20%, respectively, by the concomitant administration of alprazolam tablets in doses up to 4 mg/day. The clinical significance of these changes is unknown.
Drugs that inhibit alprazolam metabolism via cytochrome P450 3A
The initial step in alprazolam metabolism is hydroxylation catalyzed by cytochrome P450 3A (CYP3A). Drugs which inhibit this metabolic pathway may have a profound effect on the clearance of alprazolam (see CONTRAINDICATIONS and WARNINGS for additional drugs of this type).
Drugs demonstrated to be CYP3A inhibitors of possible clinical significance on the basis of clinical studies involving alprazolam (caution is recommended during coadministration with alprazolam)
Fluoxetine — Coadministration of fluoxetine with alprazolam increased the maximum plasma concentration of alprazolam by 46%, decreased clearance by 21%, increased half-life by 17%, and decreased measured psychomotor performance.
Propoxyphene — Coadministration of propoxyphene decreased the maximum plasma concentration of alprazolam by 6%, decreased clearance by 38%, and increased half-life by 58%.
Oral Contraceptives — Coadministration of oral contraceptives increased the maximum plasma concentration of alprazolam by 18%, decreased clearance by 22%, and increased half-life by 29%.
Drugs and other substances demonstrated to be CYP3A inhibitors on the basis of clinical studies involving benzodiazepines metabolized similarly to alprazolam or on the basis of in vitro studies with alprazolam or other benzodiazepines (caution is recommended during coadministration with alprazolam)
Available data from clinical studies of benzodiazepines other than alprazolam suggest a possible drug interaction with alprazolam for the following: diltiazem, isoniazid, macrolide antibiotics such as erythromycin and clarithromycin, and grapefruit juice. Data from in vitro studies of alprazolam suggest a possible drug interaction with alprazolam for the following: sertraline and paroxetine. However, data from an in vivo drug interaction study involving a single dose of alprazolam 1 mg and steady state doses of sertraline (50 to 150 mg/day) did not reveal any clinically significant changes in the pharmacokinetics of alprazolam. Data from in vitro studies of benzodiazepines other than alprazolam suggest a possible drug interaction for the following: ergotamine, cyclosporine, amiodarone, nicardipine, and nifedipine. Caution is recommended during the coadministration of any of these with alprazolam (see WARNINGS).
Drugs demonstrated to be inducers of CYP3A
Carbamazepine can increase alprazolam metabolism and therefore can decrease plasma levels of alprazolam.

Drug/Laboratory Test Interactions

Although interactions between benzodiazepines and commonly employed clinical laboratory tests have occasionally been reported, there is no consistent pattern for a specific drug or specific test.

Carcinogenesis, Mutagenesis, Impairment of Fertility

No evidence of carcinogenic potential was observed during 2-year bioassay studies of alprazolam in rats at doses up to 30 mg/kg/day (150 times the maximum recommended daily human dose of 10 mg/day) and in mice at doses up to 10 mg/kg/day (50 times the maximum recommended daily human dose).
Alprazolam was not mutagenic in the rat micronucleus test at doses up to 100 mg/kg, which is 500 times the maximum recommended daily human dose of 10 mg/day. Alprazolam also was not mutagenic in vitro in the DNA Damage/Alkaline Elution Assay or the Ames Assay.
Alprazolam produced no impairment of fertility in rats at doses up to 5 mg/kg/day, which is 25 times the maximum recommended daily human dose of 10 mg/day.

Pregnancy

Teratogenic Effects

Pregnancy Category D
(see WARNINGS section).

Nonteratogenic Effects

It should be considered that the child born of a mother who is receiving benzodiazepines may be at some risk for withdrawal symptoms from the drug during the postnatal period. Also, neonatal flaccidity and respiratory problems have been reported in children born of mothers who have been receiving benzodiazepines.

Labor and Delivery

Alprazolam has no established use in labor or delivery.

Nursing Mothers

Benzodiazepines are known to be excreted in human milk. It should be assumed that alprazolam is as well. Chronic administration of diazepam to nursing mothers has been reported to cause their infants to become lethargic and to lose weight. As a general rule, nursing should not be undertaken by mothers who must use alprazolam.

Pediatric Use

Safety and effectiveness of alprazolam in individuals below 18 years of age have not been established.

Geriatric Use

The elderly may be more sensitive to the effects of benzodiazepines. They exhibit higher plasma alprazolam concentrations due to reduced clearance of the drug as compared with a younger population receiving the same doses. The smallest effective dose of alprazolam should be used in the elderly to preclude the development of ataxia and oversedation (see CLINICAL PHARMACOLOGY and DOSAGE AND ADMINISTRATION).

ADVERSE REACTIONS

The information included in the subsection on Adverse Events Observed in Short-Term, Placebo-Controlled Trials with alprazolam extended-release tablets is based on pooled data of five 6- and 8-week placebo-controlled clinical studies in panic disorder.
Adverse event reports were elicited either by general inquiry or by checklist, and were recorded by clinical investigators using terminology of their own choosing. The stated frequencies of adverse events represent the proportion of individuals who experienced, at least once, a treatment-emergent adverse event of the type listed. An event was considered treatment emergent if it occurred for the first time or worsened during therapy following baseline evaluation. In the tables and tabulations that follow, standard MedDRA terminology (version 4.0) was used to classify reported adverse events.
Adverse Events Observed in Short-Term, Placebo-Controlled Trials of Alprazolam Extended-Release
Adverse Events Reported as Reasons for Discontinuation of Treatment in Placebo-Controlled Trials
Approximately 17% of the 531 patients who received alprazolam extended-release in placebo-controlled clinical trials for panic disorder had at least one adverse event that led to discontinuation compared to 8% of 349 placebo-treated patients. The most common events leading to discontinuation and considered to be drug-related (i.e., leading to discontinuation in at least 1% of the patients treated with alprazolam extended-release at a rate at least twice that of placebo) are shown in the following table.

Common Adverse Events Leading to Discontinuation of Treatment in Placebo-Controlled Trials

System Organ Class/ Adverse Event | Percentage of Patients Discontinuing Due to Adverse Events
System Organ Class/ Adverse Event | Alprazolam Extended-Release (n=531) | Placebo (n=349)
Nervous system disorders Sedation Somnolence Dysarthria Coordination abnormal Memory impairment | 7.5 3.2 2.1 1.9 1.5 | 0.6 0.3 0 0.3 0.3
General disorders/administration site conditions Fatigue | 1.7 | 0.6
Psychiatric disorders Depression | 2.5 | 1.2

Adverse Events Occurring at an Incidence of 1% or More Among Patients Treated with Alprazolam Extended-Release
The prescriber should be aware that adverse event incidence cannot be used to predict the incidence of adverse events in the course of usual medical practice where patient characteristics and other factors differ from those which prevailed in the clinical trials. Similarly, the cited frequencies cannot be compared with event incidence obtained from other clinical investigations involving different treatments, uses, and investigators. The cited values, however, do provide the prescribing physician with some basis for estimating the relative contribution of drug and non-drug factors to the adverse event incidence rate in the population studied.
The following table shows the incidence of treatment-emergent adverse events that occurred during 6- to 8-week placebo-controlled trials in 1% or more of patients treated with alprazolam extended-release where the incidence in patients treated with alprazolam extended-release was greater than the incidence in placebo-treated patients. The most commonly observed adverse events in panic disorder patients treated with alprazolam extended-release (incidence of 5% or greater and at least twice the incidence in placebo patients) were: sedation, somnolence, memory impairment, dysarthria, coordination abnormal, ataxia, libido decreased (see table).

Treatment-Emergent Adverse Events: Incidence in Short-Term, Placebo-Controlled Clinical Trials with Alprazolam Extended-Release

System Organ Class/Adverse Event | Percentage of Patients Reporting Adverse Event
System Organ Class/Adverse Event | Alprazolam Extended Release (n=531) | Placebo (n=349)
Nervous system disorders Sedation Somnolence Memory impairment Dysarthria Coordination abnormal Mental impairment Ataxia Disturbance in attention Balance impaired Paresthesia Dyskinesia Hypoesthesia Hypersomnia | 45.2 23 15.4 10.9 9.4 7.2 7.2 3.2 3.2 2.4 1.7 1.3 1.3 | 22.6 6 6.9 2.6 0.9 5.7 3.2 0.6 0.6 1.7 1.4 0.3 0
General disorders/administration site conditions Fatigue Lethargy | 13.9 1.7 | 9.2 0.6
Infections and infestations Influenza Upper respiratory tract infections | 2.4 1.9 | 2.3 1.7
Psychiatric disorders Depression Libido decreased Disorientation Confusion Depressed mood Anxiety | 12.1 6 1.5 1.5 1.3 1.1 | 9.2 2.3 0 0.9 0.3 0.6
Metabolism and nutrition disorders Appetite decreased Appetite increased Anorexia | 7.3 7 1.5 | 7.2 6 0
Gastrointestinal disorders Dry mouth Constipation Nausea Pharyngolaryngeal pain | 10.2 8.1 6 3.2 | 9.7 4.3 3.2 2.6
Investigations Weight increased Weight decreased | 5.1 4.3 | 4.3 3.7
Injury, poisoning, and procedural complications Road traffic accident | 1.5 | 0
Reproductive system and breast disorders Dysmenorrhea Sexual dysfunction Premenstrual syndrome | 3.6 2.4 1.7 | 2.9 1.1 0.6
Musculoskeletal and connective tissue disorders Arthralgia Myalgia Pain in limb | 2.4 1.5 1.1 | 0.6 1.1 0.3
Vascular disorders Hot flushes | 1.5 | 1.4
Respiratory, thoracic, and mediastinal disorders Dyspnea Rhinitis allergic | 1.5 1.1 | 0.3 0.6
Skin and subcutaneous tissue disorders Pruritus | 1.1 | 0.9

Other Adverse Events Observed During the Premarketing Evaluation of Alprazolam Extended-Release Tablets
Following is a list of MedDRA terms that reflect treatment-emergent adverse events reported by 531 patients with panic disorder treated with alprazolam extended-release. All potentially important reported events are included except those already listed in the above table or elsewhere in labeling, those events for which a drug cause was remote, those event terms that were so general as to be uninformative, and those events that occurred at rates similar to background rates in the general population. It is important to emphasize that, although the events reported occurred during treatment with alprazolam extended-release, they were not necessarily caused by the drug. Events are further categorized by body system and listed in order of decreasing frequency according to the following definitions: frequent adverse events are those occurring on 1 or more occasions in at least l/l00 patients; infrequent adverse events are those occurring in less than l/100 patients but at least l/1000 patients; rare events are those occurring in fewer than l/1000 patients.
Cardiac disorders: Frequent: palpitation; Infrequent: sinus tachycardia
Ear and Labyrinth disorders: Frequent: Vertigo; Infrequent: tinnitus, ear pain
Eye disorders: Frequent: blurred vision; Infrequent: mydriasis, photophobia
Gastrointestinal disorders: Frequent: diarrhea, vomiting, dyspepsia, abdominal pain; Infrequent: dysphagia, salivary hypersecretion
General disorders and administration site conditions: Frequent: malaise, weakness, chest pains; Infrequent: fall, pyrexia, thirst, feeling hot and cold, edema, feeling jittery, sluggishness, asthenia, feeling drunk, chest tightness, increased energy, feeling of relaxation, hangover, loss of control of legs, rigors
Musculoskeletal and connective tissue disorders: Frequent: back pain, muscle cramps, muscle twitching
Nervous system disorders: Frequent: headache, dizziness, tremor; Infrequent: amnesia, clumsiness, syncope, hypotonia, seizures, depressed level of consciousness, sleep apnea syndrome, sleep talking, stupor
Psychiatric system disorders: Frequent: irritability, insomnia, nervousness, derealization, libido increased, restlessness, agitation, depersonalization, nightmare; Infrequent: abnormal dreams, apathy, aggression, anger, bradyphrenia, euphoric mood, logorrhea, mood swings, dysphonia, hallucination, homicidal ideation, mania, hypomania, impulse control, psychomotor retardation, suicidal ideation
Renal and urinary disorders: Frequent: difficulty in micturition; Infrequent: urinary frequency, urinary incontinence
Respiratory, thoracic, and mediastinal disorders: Frequent: nasal congestion, hyperventilation; Infrequent: choking sensation, epistaxis, rhinorrhea
Skin and subcutaneous tissue disorders: Frequent: sweating increased; Infrequent: clamminess, rash, urticaria
Vascular disorders: Infrequent: hypotension
The categories of adverse events reported in the clinical development program for alprazolam tablets in the treatment of panic disorder differ somewhat from those reported for alprazolam extended-release tablets because the clinical trials with alprazolam tablets and alprazolam extended-release tablets used different standard medical nomenclature for reporting the adverse events. Nevertheless, the types of adverse events reported in the clinical trials with alprazolam tablets were generally the same as those reported in the clinical trials with alprazolam extended-release tablets.
Discontinuation-Emergent Adverse Events Occurring at an Incidence of 5% or More Among Patients Treated with Alprazolam Extended-Release
The following table shows the incidence of discontinuation-emergent adverse events that occurred during short-term, placebo-controlled trials in 5% or more of patients treated with alprazolam extended-release where the incidence in patients treated with alprazolam extended-release was two times greater than the incidence in placebo-treated patients.

Discontinuation-Emergent Symptoms: Incidence in Short-Term, Placebo-Controlled Trials with Alprazolam Extended-Release

System Organ Class/ Adverse Event | Percentage of Patients Reporting Adverse Event
System Organ Class/ Adverse Event | Alprazolam Extended Release (n=422) | Placebo (n=261)
Nervous system disorders Tremor Headache Hypoesthesia Paresthesia | 28.2 26.5 7.8 7.1 | 10.7 12.6 2.3 2.7
Psychiatric disorders Insomnia Nervousness Depression Derealization Anxiety Depersonalization | 24.2 21.8 10.9 8 7.8 5.7 | 9.6 8.8 5 3.8 2.7 1.9
Gastrointestinal disorders Diarrhea | 12.1 | 3.1
Respiratory, thoracic and mediastinal disorders Hyperventilation | 8.5 | 2.7
Metabolism and nutrition disorders Appetite decreased | 9.5 | 3.8
Musculoskeletal and connective tissue disorders Muscle twitching | 7.4 | 2.7
Vascular disorders Hot flushes | 5.9 | 2.7

There have also been reports of withdrawal seizures upon rapid decrease or abrupt discontinuation of alprazolam (see WARNINGS).
To discontinue treatment in patients taking alprazolam extended-release tablets, the dosage should be reduced slowly in keeping with good medical practice. It is suggested that the daily dosage of alprazolam extended-release tablets be decreased by no more than 0.5 mg every three days (see DOSAGE AND ADMINISTRATION). Some patients may benefit from an even slower dosage reduction. In a controlled postmarketing discontinuation study of panic disorder patients which compared this recommended taper schedule with a slower taper schedule, no difference was observed between the groups in the proportion of patients who tapered to zero dose; however, the slower schedule was associated with a reduction in symptoms associated with a withdrawal syndrome.
As with all benzodiazepines, paradoxical reactions such as stimulation, increased muscle spasticity, sleep disturbances, hallucinations, and other adverse behavioral effects such as agitation, rage, irritability, and aggressive or hostile behavior have been reported rarely. In many of the spontaneous case reports of adverse behavioral effects, patients were receiving other CNS drugs concomitantly and/or were described as having underlying psychiatric conditions. Should any of the above events occur, alprazolam should be discontinued. Isolated published reports involving small numbers of patients have suggested that patients who have borderline personality disorder, a prior history of violent or aggressive behavior, or alcohol or substance abuse may be at risk for such events. Instances of irritability, hostility, and intrusive thoughts have been reported during discontinuation of alprazolam in patients with posttraumatic stress disorder.
Post Introduction Reports
Various adverse drug reactions have been reported in association with the use of alprazolam tablets since market introduction. The majority of these reactions were reported through the medical event voluntary reporting system. Because of the spontaneous nature of the reporting of medical events and the lack of controls, a causal relationship to the use of alprazolam tablets cannot be readily determined. Reported events include: gastrointestinal disorder, hypomania, mania, liver enzyme elevations, hepatitis, hepatic failure, Stevens-Johnson syndrome, angioedema, peripheral edema, hyperprolactinemia, gynecomastia, and galactorrhea (see PRECAUTIONS).

DRUG ABUSE AND DEPENDENCE

Physical and Psychological Dependence
Withdrawal symptoms similar in character to those noted with sedative/hypnotics and alcohol have occurred following discontinuance of benzodiazepines, including alprazolam. The symptoms can range from mild dysphoria and insomnia to a major syndrome that may include abdominal and muscle cramps, vomiting, sweating, tremors, and convulsions. Distinguishing between withdrawal emergent signs and symptoms and the recurrence of illness is often difficult in patients undergoing dose reduction. The long-term strategy for treatment of these phenomena will vary with their cause and the therapeutic goal. When necessary, immediate management of withdrawal symptoms requires re-institution of treatment at doses of alprazolam sufficient to suppress symptoms. There have been reports of failure of other benzodiazepines to fully suppress these withdrawal symptoms. These failures have been attributed to incomplete cross-tolerance but may also reflect the use of an inadequate dosing regimen of the substituted benzodiazepine or the effects of concomitant medications.
While it is difficult to distinguish withdrawal and recurrence for certain patients, the time course and the nature of the symptoms may be helpful. A withdrawal syndrome typically includes the occurrence of new symptoms, tends to appear toward the end of taper or shortly after discontinuation, and will decrease with time. In recurring panic disorder, symptoms similar to those observed before treatment may recur either early or late, and they will persist.
While the severity and incidence of withdrawal phenomena appear to be related to dose and duration of treatment, withdrawal symptoms, including seizures, have been reported after only brief therapy with alprazolam at doses within the recommended range for the treatment of anxiety (e.g., 0.75 to 4 mg/day). Signs and symptoms of withdrawal are often more prominent after rapid decrease of dosage or abrupt discontinuance. The risk of withdrawal seizures may be increased at doses above 4 mg/day (see WARNINGS).
Patients, especially individuals with a history of seizures or epilepsy, should not be abruptly discontinued from any CNS depressant agent, including alprazolam. It is recommended that all patients on alprazolam who require a dosage reduction be gradually tapered under close supervision (see WARNINGS and DOSAGE AND ADMINISTRATION).
Psychological dependence is a risk with all benzodiazepines, including alprazolam. The risk of psychological dependence may also be increased at doses greater than 4 mg/day and with longer term use, and this risk is further increased in patients with a history of alcohol or drug abuse. Some patients have experienced considerable difficulty in tapering and discontinuing from alprazolam, especially those receiving higher doses for extended periods. Addiction-prone individuals should be under careful surveillance when receiving alprazolam. As with all anxiolytics, repeat prescriptions should be limited to those who are under medical supervision.
Controlled Substance Class
Alprazolam is a controlled substance under the Controlled Substance Act by the Drug Enforcement Administration and alprazolam extended-release tablets have been assigned to Schedule IV.

OVERDOSAGE

Clinical Experience
Overdosage reports with alprazolam tablets are limited. Manifestations of alprazolam overdosage include somnolence, confusion, impaired coordination, diminished reflexes, and coma. Death has been reported in association with overdoses of alprazolam by itself, as it has with other benzodiazepines. In addition, fatalities have been reported in patients who have overdosed with a combination of a single benzodiazepine, including alprazolam, and alcohol; alcohol levels seen in some of these patients have been lower than those usually associated with alcohol-induced fatality.
Animal experiments have suggested that forced diuresis or hemodialysis are probably of little value in treating overdosage.
General Treatment of Overdose
As in all cases of drug overdosage, respiration, pulse rate, and blood pressure should be monitored. General supportive measures should be employed, along with immediate gastric lavage. Intravenous fluids should be administered and an adequate airway maintained. If hypotension occurs, it may be combated by the use of vasopressors. Dialysis is of limited value. As with the management of intentional overdosing with any drug, it should be borne in mind that multiple agents may have been ingested.
Flumazenil, a specific benzodiazepine receptor antagonist, is indicated for the complete or partial reversal of the sedative effects of benzodiazepines and may be used in situations when an overdose with a benzodiazepine is known or suspected. Prior to the administration of flumazenil, necessary measures should be instituted to secure airway, ventilation, and intravenous access. Flumazenil is intended as an adjunct to, not as a substitute for, proper management of benzodiazepine overdose. Patients treated with flumazenil should be monitored for re-sedation, respiratory depression, and other residual benzodiazepine effects for an appropriate period after treatment. The prescriber should be aware of a risk of seizure in association with flumazenil treatment, particularly in long-term benzodiazepine users and in cyclic antidepressant overdose. The complete flumazenil package insert including CONTRAINDICATIONS, WARNINGS, and PRECAUTIONS should be consulted prior to use.

DOSAGE AND ADMINISTRATION

Alprazolam extended-release tablets may be administered once daily, preferably in the morning. The tablets should be taken intact; they should not be chewed, crushed, or broken.
The suggested total daily dose ranges between 3 to 6 mg/day. Dosage should be individualized for maximum beneficial effect. While the suggested total daily dosages given will meet the needs of most patients, there will be some patients who require doses greater than 6 mg/day. In such cases, dosage should be increased cautiously to avoid adverse effects.
Dosing in Special Populations
In elderly patients, in patients with advanced liver disease, or in patients with debilitating disease, the usual starting dose of alprazolam extended-release tablets is 0.5 mg once daily. This may be gradually increased if needed and tolerated (see Dose Titration). The elderly may be especially sensitive to the effects of benzodiazepines.

Dose Titration

Treatment with alprazolam extended-release tablets may be initiated with a dose of 0.5 mg to 1 mg once daily. Depending on the response, the dose may be increased at intervals of 3 to 4 days in increments of no more than 1 mg/day. Slower titration to the dose levels may be advisable to allow full expression of the pharmacodynamic effect of alprazolam extended-release tablets.
Generally, therapy should be initiated at a low dose to minimize the risk of adverse responses in patients especially sensitive to the drug. Dose should be advanced until an acceptable therapeutic response (i.e., a substantial reduction in or total elimination of panic attacks) is achieved, intolerance occurs, or the maximum recommended dose is attained.
Dose Maintenance
In controlled trials conducted to establish the efficacy of alprazolam extended-release tablets in panic disorder, doses in the range of 1 to 10 mg/day were used. Most patients showed efficacy in the dose range of 3 to 6 mg/day. Occasional patients required as much as 10 mg/day to achieve a successful response.
The necessary duration of treatment for panic disorder patients responding to alprazolam extended-release tablets is unknown. However, periodic reassessment is advised. After a period of extended freedom from attacks, a carefully supervised tapered discontinuation may be attempted, but there is evidence that this may often be difficult to accomplish without recurrence of symptoms and/or the manifestation of withdrawal phenomena.
Dose Reduction
Because of the danger of withdrawal, abrupt discontinuation of treatment should be avoided (see WARNINGS, PRECAUTIONS, and DRUG ABUSE AND DEPENDENCE).
In all patients, dosage should be reduced gradually when discontinuing therapy or when decreasing the daily dosage. Although there are no systematically collected data to support a specific discontinuation schedule, it is suggested that the daily dosage be decreased by no more than 0.5 mg every three days. Some patients may require an even slower dosage reduction.
In any case, reduction of dose must be undertaken under close supervision and must be gradual. If significant withdrawal symptoms develop, the previous dosing schedule should be reinstituted and, only after stabilization, should a less rapid schedule of discontinuation be attempted. In a controlled postmarketing discontinuation study of panic disorder patients which compared this recommended taper schedule with a slower taper schedule, no difference was observed between the groups in the proportion of patients who tapered to zero dose; however, the slower schedule was associated with a reduction in symptoms associated with a withdrawal syndrome. It is suggested that the dose be reduced by no more than 0.5 mg every three days, with the understanding that some patients may benefit from an even more gradual discontinuation. Some patients may prove resistant to all discontinuation regimens.
Switch from Alprazolam (Immediate-Release) Tablets to Alprazolam Extended-Release Tablets
Patients who are currently being treated with divided doses of alprazolam (immediate-release) tablets, for example 3 to 4 times a day, may be switched to alprazolam extended-release tablets at the same total daily dose taken once daily. If the therapeutic response after switching is inadequate, the dosage may be titrated as outlined above.

HOW SUPPLIED

Alprazolam Extended-Release Tablets USP, 0.5 mg are white to off-white, round, biconvex tablets with beveled edge debossed with ‘X’ on one side and ‘70’ on the other side.
Bottles of 30 NDC 63187-518-30
Bottles of 60 NDC 63187-518-60
Bottles of 90 NDC 63187-518-90
Store at 20° to 25°C (68° to 77°F); excursions permitted to 15° to 30°C (59° to 86°F) [see USP Controlled Room Temperature].

ANIMAL STUDIES

When rats were treated with alprazolam at 3, 10, and 30 mg/kg/day (15 to 150 times the maximum recommended human dose) orally for 2 years, a tendency for a dose related increase in the number of cataracts was observed in females and a tendency for a dose related increase in corneal vascularization was observed in males. These lesions did not appear until after 11 months of treatment.
Manufactured for:
Aurobindo Pharma USA, Inc.
2400 Route 130 North
Dayton, NJ 08810
Manufactured by:
Aurobindo Pharma Limited
Hyderabad-500 072, India
Revised: 11/2013

Repackaged by:

Proficient Rx LP

Thousand Oaks, CA 91320

PACKAGE LABEL-PRINCIPAL DISPLAY PANEL - 0.5 mg (60 Tablet Bottle)

NDC 63187-518-60
Alprazolam Extended-Release
Tablets USP 0.5 mg CIV
Rx only 60 Tablets